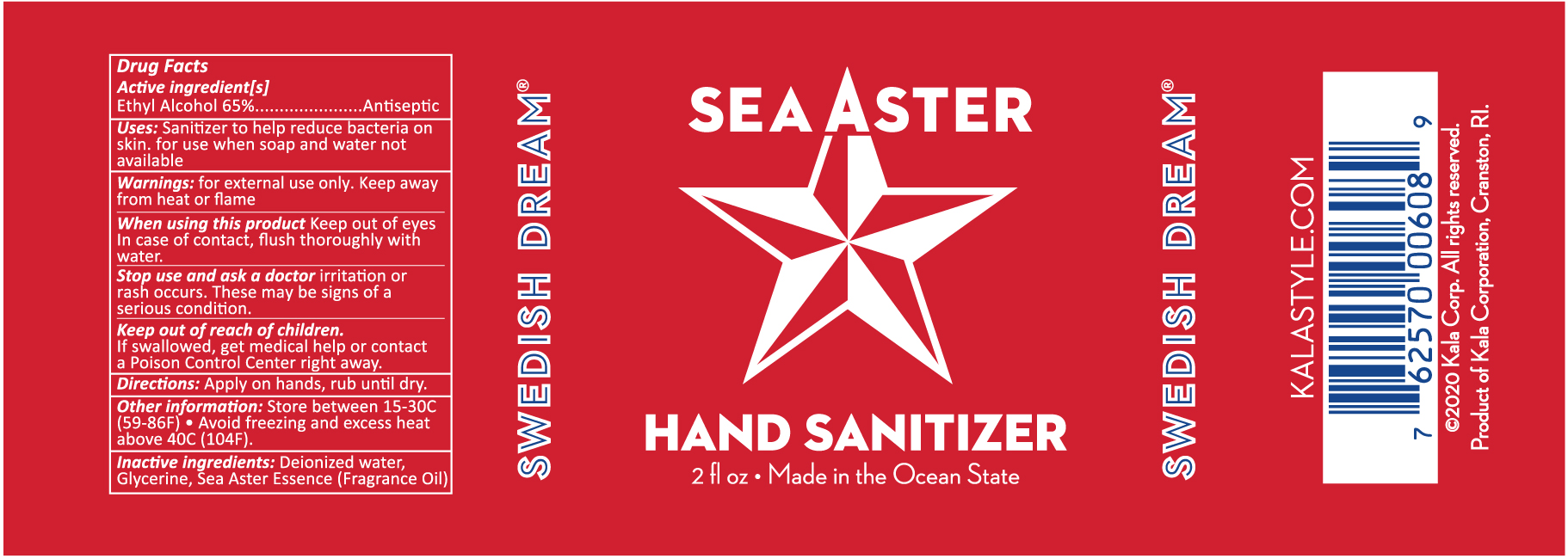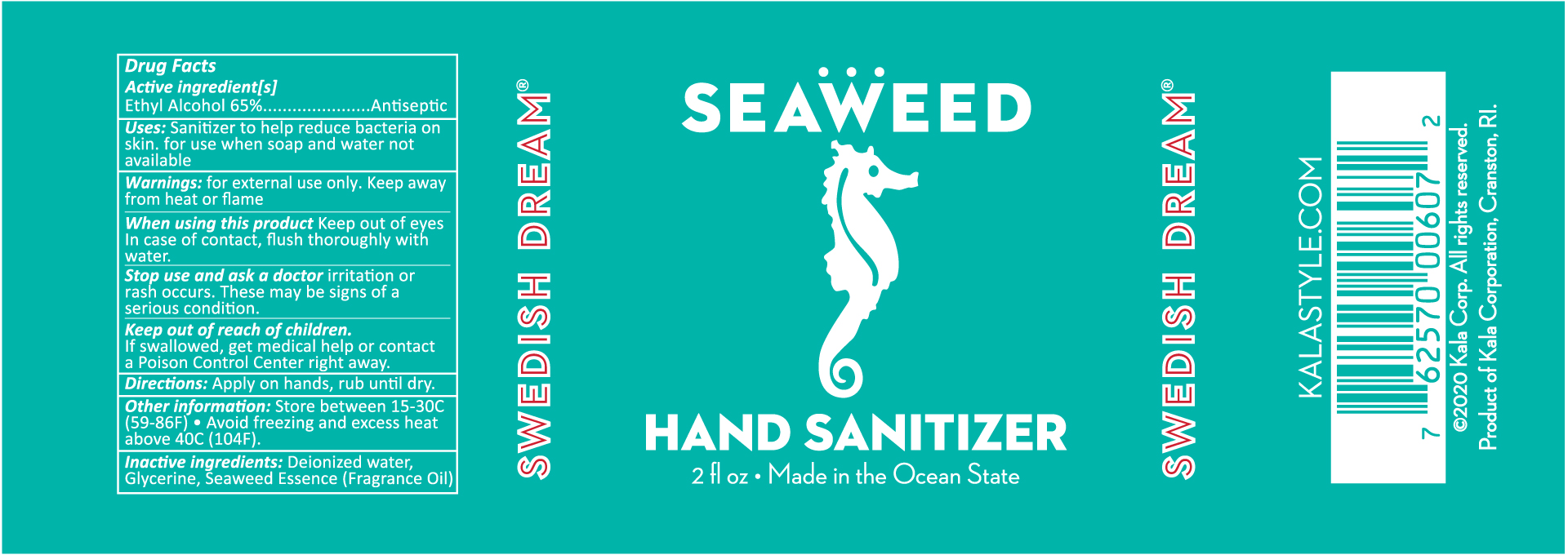 DRUG LABEL: Swedish Dream Seaweed Hand Sanitizer
NDC: 79655-607 | Form: SPRAY
Manufacturer: Kala Corporation
Category: otc | Type: HUMAN OTC DRUG LABEL
Date: 20220113

ACTIVE INGREDIENTS: ALCOHOL 38.35 mL/59 mL
INACTIVE INGREDIENTS: WATER 19.65 mL/59 mL; PARA-CRESOL 0.08 mL/59 mL; ACETOPHENONE 0.1 mL/59 mL; GLYCERIN 0.8 mL/59 mL; BENZYL ACETATE 0.1 mL/59 mL; HEXYLENE GLYCOL 0.1 mL/59 mL

Swedish Dream® Seaweed and Sea Aster Hand Sanitizer

Drug Facts

Active Ingredient[s]

Ethyl Alcohol 65%

Purpose

Antiseptic

Uses

Sanitizer to help reduce bacteria on skin. For use when soap and water not available

Warnings

for external use only. Keep away from heat or flame

When using this product

Keep out of eyes In case of contact, flush thoroughly with water.

Stop use and ask a doctor

irritation or rash occurs. These may be signs of a serious condition.

Keep out of reach of children

If swallowed, get medical help or contact a Poison Control Center right away.

Directions

Apply on hands, rub until dry.

Other information:

Store between 15-30C (59-86F) • Avoid freezing and excess heat above 40C (104F).

Inactive Ingredients

Deionized water, Glycerine, Fragrance Oil